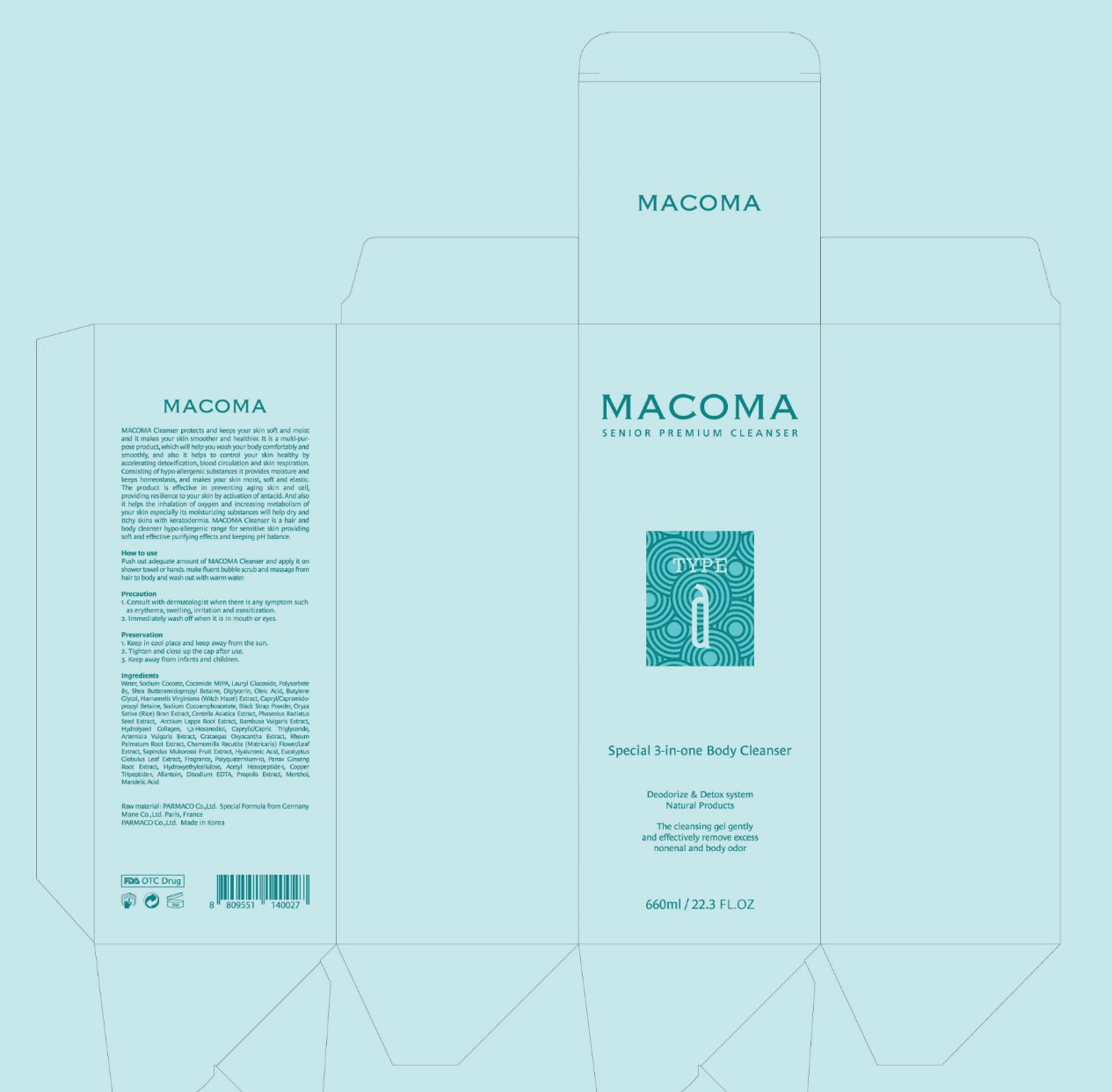 DRUG LABEL: Macoma Senior Premium Cleanser
NDC: 71614-003 | Form: GEL
Manufacturer: PARMA KOREA.CO.LTD
Category: otc | Type: HUMAN OTC DRUG LABEL
Date: 20230104

ACTIVE INGREDIENTS: ALLANTOIN 10 mg/1 mL
INACTIVE INGREDIENTS: WATER; LAURAMIDOPROPYL BETAINE; HYALURONIC ACID; SODIUM COCOAMPHOACETATE; HYMETELLOSE (50 MPA.S); ACETYL HEXAPEPTIDE-8; EDETATE DISODIUM ANHYDROUS; LAURYL GLUCOSIDE; BETULA PUBESCENS RESIN; BLACK OLIVE; TREHALOSE; CENTELLA ASIATICA; BUTYLENE GLYCOL; DIGLYCERIN; RICE BRAN; HAMAMELIS VIRGINIANA TOP; BAMBUSA VULGARIS TOP; TURMERIC; ARTEMISIA VULGARIS ROOT; ARCTIUM LAPPA ROOT; HIPPOPHAE RHAMNOIDES FRUIT; RHEUM PALMATUM ROOT; EUCALYPTUS GLOBULUS LEAF; BERGAMOT OIL; LAVANDULA ANGUSTIFOLIA SUBSP. ANGUSTIFOLIA FLOWER; SAPINDUS MUKOROSSI FRUIT; ASIAN GINSENG; MENTHA PIPERITA; PROPOLIS WAX; MANDELIC ACID; .ALPHA.-TOCOPHEROL ACETATE; ASCORBIC ACID; POLYSORBATE 85; 1,2-HEXANEDIOL; MEDIUM-CHAIN TRIGLYCERIDES

71614-003_Macoma Senior Premium Cleanser

ACTIVE INGREDIENT

Allantoin 1%

PURPOSE

Deodorizing cleansing gel

INDICATIONS AND USAGE

Body Cleansing

DOSAGE AND ADMINISTRATION

Push out adequate amount of MACOMA Cleanser and apply it on shower towel or hands. Make fluent bubble scrub and massage from hair to body and wash out with warm water.

WARNINGS

Consult with dermatologiest when there is any symptom such as erythema, swelling, irritation and esnsitization.

Immediately wash off when it is in mouth or eyes.

Keep out of reach of children

INACTIVE INGREDIENT

Water
Lauramidopropyl Betaine
Hyaluronic Acid
Sodium Cocoamphoacetate
Methyl Hydroxyethylcellulose
Acetyl Hexapeptide-8
Disodium EDTA
Lauryl Glucoside
Betula Alba Juice
Olea Europaea (Olive) Fruit Extract
Hydrolyzed Collagen
Trehalose
Centella Asiatica Extract
Butylene Glycol
Diglycerin
Oryza Sativa (Rice) Bran Extract
Hamamelis Virginiana (Witch Hazel) Extract
Bambusa Vulgaris Extract
Curcuma Longa (Turmeric) Root Extract
Artemisia Vulgaris Extract
Arctium Lappa Root Extract
Hippophae Rhamnoides Extract
Rheum Palmatum Root Extract
Eucalyptus Globulus Leaf Extract
Citrus Aurantium Bergamia (Bergamot) Fruit Extract
Lavandula Angustifolia (Lavender) Flower Extract
Sapindus Mukorossi Fruit Extract
Pelargonium Graveolens Extract
Panax Ginseng Root Extract
Mentha Piperita (Peppermint) Extract
Propolis Extract
Mandelic Acid
Tocopheryl Acetate
Ascorbic Acid
Polysorbate 85
1,2-Hexanediol
Caprylic/Capric Triglyceride